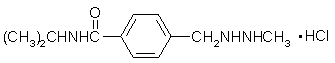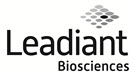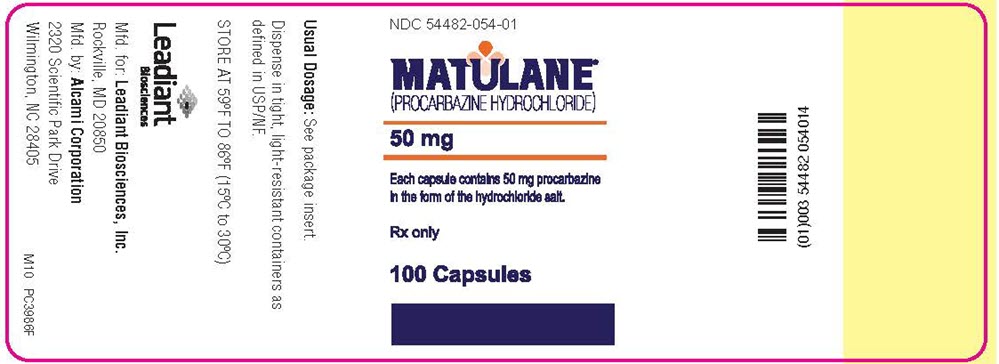 DRUG LABEL: Matulane
NDC: 54482-054 | Form: CAPSULE
Manufacturer: Leadiant Biosciences, Inc.
Category: prescription | Type: HUMAN PRESCRIPTION DRUG LABEL
Date: 20240916

ACTIVE INGREDIENTS: PROCARBAZINE HYDROCHLORIDE 50 mg/1 1
INACTIVE INGREDIENTS: STARCH, CORN; MANNITOL; TALC; GELATIN, UNSPECIFIED; TITANIUM DIOXIDE; FD&C YELLOW NO. 6; D&C YELLOW NO. 10

MATULANE ®(procarbazine hydrochloride) Capsules

WARNING

It is recommended that MATULANE be given only by or under the supervision of a physician experienced in the use of potent antineoplastic drugs. Adequate clinical and laboratory facilities should be available to patients for proper monitoring of treatment.

DESCRIPTION

Matulane (procarbazine hydrochloride), a hydrazine derivative antineoplastic agent, is available as capsules containing the equivalent of 50 mg procarbazine as the hydrochloride. Each capsule also contains cornstarch, mannitol and talc. Gelatin capsule shells contain titanium dioxide, FD&C Yellow No. 6 and D&C Yellow No. 10.

Chemically, procarbazine hydrochloride is N‑isopropyl-∝-(2‑methylhydrazino)‑p‑toluamide monohydrochloride. It is a white to pale yellow crystalline powder which is soluble but unstable in water or aqueous solutions. The molecular weight of procarbazine hydrochloride is 257.76 and the structural formula is:

CLINICAL PHARMACOLOGY

The precise mode of cytotoxic action of procarbazine has not been clearly defined. There is evidence that the drug may act by inhibition of protein, RNA and DNA synthesis. Studies have suggested that procarbazine may inhibit transmethylation of methyl groups of methionine into t‑RNA. The absence of functional t‑RNA could cause the cessation of protein synthesis and consequently DNA and RNA synthesis. In addition, procarbazine may directly damage DNA. Hydrogen peroxide, formed during the auto‑oxidation of the drug, may attack protein sulfhydryl groups contained in residual protein which is tightly bound to DNA.

Procarbazine is metabolized primarily in the liver and kidneys. The drug appears to be auto-oxidized to the azo derivative with the release of hydrogen peroxide. The azo derivative isomerizes to the hydrazone, and following hydrolysis splits into a benzylaldehyde derivative and methylhydrazine. The methylhydrazine is further degraded to CO2 and CH4 and possibly hydrazine, whereas the aldehyde is oxidized to N-isopropylterephthalamic acid, which is excreted in the urine.

Procarbazine is rapidly and completely absorbed. Following oral administration of 30 mg of ^14C-labeled procarbazine, maximum peak plasma radioactive concentrations were reached within 60 minutes.

After intravenous injection, the plasma half-life of procarbazine is approximately 10 minutes. Approximately 70% of the radioactivity is excreted in the urine as N-isopropylterephthalamic acid within 24 hours following both oral and intravenous administration of ^14C-labeled procarbazine.

Procarbazine crosses the blood-brain barrier and rapidly equilibrates between plasma and cerebrospinal fluid after oral administration.

INDICATIONS AND USAGE

Matulane is indicated for use in combination with other anticancer drugs for the treatment of Stage III and IV Hodgkin's disease. Matulane is used as part of the MOPP (nitrogen mustard, vincristine, procarbazine, prednisone) regimen.

CONTRAINDICATIONS

Matulane is contraindicated in patients with known hypersensitivity to the drug or inadequate marrow reserve as demonstrated by bone marrow aspiration. Due consideration of this possible state should be given to each patient who has leukopenia, thrombocytopenia or anemia.

WARNINGS

To minimize CNS depression and possible potentiation, barbiturates, antihistamines, narcotics, hypotensive agents or phenothiazines should be used with caution. Ethyl alcohol should not be used since there may be an Antabuse (disulfiram)-like reaction. Because Matulane exhibits some monoamine oxidase inhibitory activity, sympathomimetic drugs, tricyclic antidepressant drugs (eg, amitriptyline HCI, imipramine HCI) and other drugs and foods with known high tyramine content, such as wine, yogurt, ripe cheese and bananas, should be avoided. A further phenomenon of toxicity common to many hydrazine derivatives is hemolysis and the appearance of Heinz‑Ehrlich inclusion bodies in erythrocytes.

Pregnancy

Teratogenic Effects

Procarbazine hydrochloride can cause fetal harm when administered to a pregnant woman. While there are no adequate and well‑controlled studies with procarbazine hydrochloride in pregnant women, there are case reports of malformations in the offspring of women who were exposed to procarbazine hydrochloride in combination with other antineoplastic agents during pregnancy. Matulane should be used during pregnancy only if the potential benefit justifies the potential risk to the fetus. If this drug is used during pregnancy, or if the patient becomes pregnant while taking this drug, the patient should be apprised of the potential hazard to the fetus. Women of childbearing potential should be advised to avoid becoming pregnant. Procarbazine hydrochloride is teratogenic in the rat when given at doses approximately 4 to 13 times the maximum recommended human therapeutic dose of 6 mg/kg/day.

Nonteratogenic Effects

Procarbazine hydrochloride has not been adequately studied in animals for its effects on peri- and postnatal development. However, neurogenic tumors were noted in the offspring of rats given intravenous injections of 125 mg/kg of procarbazine hydrochloride on day 22 of gestation. Compounds which inhibit DNA, RNA and protein synthesis might be expected to have adverse effects on peri- and postnatal development.

Carcinogenesis, Mutagenesis, Impairment of Fertility

Carcinogenesis

The carcinogenicity of procarbazine hydrochloride in mice, rats and monkeys has been reported in a considerable number of studies. Instances of a second nonlymphoid malignancy, including lung cancer and acute myelocytic leukemia, have been reported in patients with Hodgkin's disease treated with procarbazine in combination with other chemotherapy and/or radiation. The risks of secondary lung cancer from treatment appear to be multiplied by tobacco use. The International Agency for Research on Cancer (IARC) considers that there is "sufficient evidence" for the human carcinogenicity of procarbazine hydrochloride when it is given in intensive regimens which include other antineoplastic agents but that there is inadequate evidence of carcinogenicity in humans given procarbazine hydrochloride alone.

Mutagenesis

Procarbazine hydrochloride has been shown to be mutagenic in a variety of bacterial and mammalian test systems.

Impairment of Fertility

Azoospermia and antifertility effects associated with procarbazine hydrochloride administration in combination with other chemotherapeutic agents for treating Hodgkin's disease have been reported in human clinical studies. Since these patients received multicombination therapy, it is difficult to determine to what extent procarbazine hydrochloride alone was involved in the male germcell damage. The usual Segment I fertility/reproduction studies in laboratory animals have not been carried out with procarbazine hydrochloride. However, compounds which inhibit DNA, RNA and/or protein synthesis might be expected to have adverse effects on gametogenesis. Unscheduled DNA synthesis in the testis of rabbits and decreased fertility in male mice treated with procarbazine hydrochloride have been reported.

PRECAUTIONS

General

Undue toxicity may occur if Matulane is used in patients with impairment of renal and/or hepatic function. When appropriate, hospitalization for the initial course of treatment should be considered.

If radiation or a chemotherapeutic agent known to have marrow-depressant activity has been used, an interval of one month or longer without such therapy is recommended before starting treatment with Matulane. The length of this interval may also be determined by evidence of bone marrow recovery based on successive bone marrow studies.

Prompt cessation of therapy is recommended if any one of the following occurs:

- Central nervous system signs or symptoms such as paresthesias, neuropathies or confusion.
- Leukopenia (white blood count under 4000).
- Thrombocytopenia (platelets under 100,000).
- Hypersensitivity reaction.
- Stomatitis - The first small ulceration or persistent spot soreness around the oral cavity is a signal for cessation of therapy.
- Diarrhea - Frequent bowel movements or watery stools.
- Hemorrhage or bleeding tendencies.

Bone marrow depression often occurs 2 to 8 weeks after the start of treatment. If leukopenia occurs, hospitalization of the patient may be needed for appropriate treatment to prevent systemic infection.

Information for Patients

Patients should be warned not to drink alcoholic beverages while on Matulane therapy since there may be an Antabuse (disulfiram)‑like reaction. They should also be cautioned to avoid foods with known high tyramine content such as wine, yogurt, ripe cheese and bananas. Over-the-counter drug preparations which contain antihistamines or sympathomimetic drugs should also be avoided. Patients taking Matulane should also be warned against the use of prescription drugs without the knowledge and consent of their physician. Patients should be advised to discontinue tobacco use.

Laboratory Tests

Baseline laboratory data should be obtained prior to initiation of therapy. The hematologic status as indicated by hemoglobin, hematocrit, white blood count (WBC), differential, reticulocytes and platelets should be monitored closely - at least every 3 or 4 days.

Hepatic and renal evaluation are indicated prior to beginning therapy. Urinalysis, transaminase, alkaline phosphatase and blood urea nitrogen tests should be repeated at least weekly.

Drug Interactions

See WARNINGS section.

No cross-resistance with other chemotherapeutic agents, radiotherapy or steroids has been demonstrated.

Carcinogenesis, Mutagenesis, Impairment of Fertility

See WARNINGS section.

Pregnancy

See WARNINGS section.

Nursing Mothers

It is not known whether Matulane is excreted in human milk. Because of the potential for tumorigenicity shown for procarbazine hydrochloride in animal studies, mothers should not nurse while receiving this drug.

Pediatric Use

Undue toxicity, evidenced by tremors, coma and convulsions, has occurred in a few cases. Dosage, therefore, should be individualized (see DOSAGE AND ADMINISTRATION). Very close clinical monitoring is mandatory.

ADVERSE REACTIONS

Leukopenia, anemia and thrombopenia occur frequently. Nausea and vomiting are the most commonly reported side effects.

Other adverse reactions are:

Hematologic

Pancytopenia; eosinophilia; hemolytic anemia; bleeding tendencies such as petechiae, purpura, epistaxis and hemoptysis.

Gastrointestinal

Hepatic dysfunction, jaundice, stomatitis, hematemesis, melena, diarrhea, dysphagia, anorexia, abdominal pain, constipation, dry mouth.

Neurologic

Coma, convulsions, neuropathy, ataxia, paresthesia, nystagmus, diminished reflexes, falling, foot drop, headache, dizziness, unsteadiness.

Cardiovascular

Hypotension, tachycardia, syncope.

Ophthalmic

Retinal hemorrhage, papilledema, photophobia, diplopia, inability to focus.

Respiratory

Pneumonitis, pleural effusion, cough.

Dermatologic

Herpes, dermatitis, pruritus, alopecia, hyperpigmentation, rash, urticaria, flushing.

Allergic

Generalized allergic reactions.

Genitourinary

Hematuria, urinary frequency, nocturia.

Musculoskeletal

Pain, including myalgia and arthralgia; tremors.

Psychiatric

Hallucinations, depression, apprehension, nervousness, confusion, nightmares.

Endocrine

Gynecomastia in prepubertal and early pubertal boys.

Miscellaneous

Intercurrent infections, hearing loss, pyrexia, diaphoresis, lethargy, weakness, fatigue, edema, chills, insomnia, slurred speech, hoarseness, drowsiness.

Second nonlymphoid malignancies (including lung cancer, acute myelocytic leukemia and malignant myelosclerosis) and azoospermia have been reported in patients with Hodgkin's disease treated with procarbazine in combination with other chemotherapy and/or radiation. The risks of secondary lung cancer from treatment appear to be multiplied by tobacco use.

OVERDOSAGE

The major manifestations of overdosage with Matulane would be anticipated to be nausea, vomiting, enteritis, diarrhea, hypotension, tremors, convulsions and coma. Treatment should consist of either the administration of an emetic or gastric lavage. General supportive measures such as intravenous fluids are advised. Since the major toxicity of procarbazine hydrochloride is hematologic and hepatic, patients should have frequent complete blood counts and liver function tests throughout their period of recovery and for a minimum of two weeks thereafter. Should abnormalities appear in any of these determinations, appropriate measures for correction and stabilization should be immediately undertaken.

The estimated mean lethal dose of procarbazine hydrochloride in laboratory animals varied from approximately 150 mg/kg in rabbits to 1300 mg/kg in mice.

DOSAGE AND ADMINISTRATION

The following doses are for administration of the drug as a single agent. When used in combination with other anticancer drugs, the Matulane dose should be appropriately reduced, eg, in the MOPP regimen, the Matulane dose is 100 mg/m2 daily for 14 days. All dosages are based on the patient's actual weight. However, the estimated lean body mass (dry weight) is used if the patient is obese or if there has been a spurious weight gain due to edema, ascites or other forms of abnormal fluid retention.

Adults:To minimize the nausea and vomiting experienced by a high percentage of patients beginning Matulane therapy, single or divided doses of 2 to 4 mg/kg/day for the first week are recommended. Daily dosage should then be maintained at 4 to 6 mg/kg/day until maximum response is obtained or until the white blood count falls below 4000/cmm or the platelets fall below 100,000/ cmm. When maximum response is obtained, the dose may be maintained at 1 to 2 mg/kg/day. Upon evidence of hematologic or other toxicity (see PRECAUTIONS section), the drug should be discontinued until there has been satisfactory recovery. After toxic side effects have subsided, therapy may then be resumed at the discretion of the physician, based on clinical evaluation and appropriate laboratory studies, at a dosage of 1 to 2 mg/kg/day.

Pediatric Patients:Very close clinical monitoring is mandatory. Undue toxicity, evidenced by tremors, coma and convulsions, has occurred in a few cases. Dosage, therefore, should be individualized. The following dosage schedule is provided as a guideline only.

Fifty (50) mg per square meter of body surface per day is recommended for the first week. Dosage should then be maintained at 100 mg per square meter of body surface per day until maximum response is obtained or until leukopenia or thrombocytopenia occurs. When maximum response is attained, the dose may be maintained at 50 mg per square meter of body surface per day. Upon evidence of hematologic or other toxicity (see PRECAUTIONS section), the drug should be discontinued until there has been satisfactory recovery, based on clinical evaluation and appropriate laboratory tests. After toxic side effects have subsided, therapy may then be resumed.

Procedures for proper handling and disposal of anticancer drugs should be considered. Several guidelines on this subject have been published.^1-6There is no general agreement that all of the procedures recommended in the guidelines are necessary or appropriate.

HOW SUPPLIED

Capsules, ivory, containing the equivalent of 50 mg procarbazine as the hydrochloride; in bottles of 100 (NDC 54482-054-01). Imprint on capsules: MATULANE LB213.

REFERENCES

1. Recommendations for the safe handling of parenteral antineoplastic drugs. Washington, DC: U.S. Government Printing Office NIH Publication No. 83-2621.
2. AMA Council Report. Guidelines for handling parenteral antineoplastics.JAMA. Mar 15, 1985; 253:1590-1592.
3. National Study Commission on Cytotoxic Exposure: Recommendations for handling cytotoxic agents. Available from Louis P. Jeffrey, ScD, Director of Pharmacy Services, Rhode Island Hospital, 593 Eddy Street, Providence, Rhode Island 02902.
4. Clinical Oncological Society of Australia: Guidelines and recommendations for safe handling of antineoplastic agents.Med J Aust.Apr 30,1983; 1:426-428.
5. Jones RB, Frank R, Mass T: Safe handling of chemotherapeutic agents: a report from the Mount Sinai Medical Center.CA.Sept-Oct 1983; 33:258-263.
6. ASHP technical assistance bulletin on handling cytotoxic drugs in hospitals.Am J Hosp Pharm.Jan 1985; 42:131-137.

Manufactured by
Alcami Corporation
1726 North 23rd St.
Wilmington, NC 28405
forLeadiant Biosciences, Inc.
Rockville, MD 20850

Revised: November 2023
MAT12

Printed in U.S.A.

PRINCIPAL DISPLAY PANEL - BOTTLE LABEL

NDC 54482-054-01

MATULANE®
(PROCARBAZINE HYDROCHLORIDE)

50 mg

Each capsule contains 50 mg procarbazine
in the form of the hydrochloride salt.

Rx only

100 Capsules

Usual Dosage:See package insert.

Dispense in tight, light-resistant containers as
defined in USP/NF.

STORE AT 59° TO 86°F (15° to 30°C)

Leadiant
Biosciences

Mfd. for Leadiant Biosciences, Inc.
Rockville, MD 20850
Mfd. by: Alcami Corporation
2320 Scientific Park Drive
Wilmington, NC 28405 M10 PC3986F